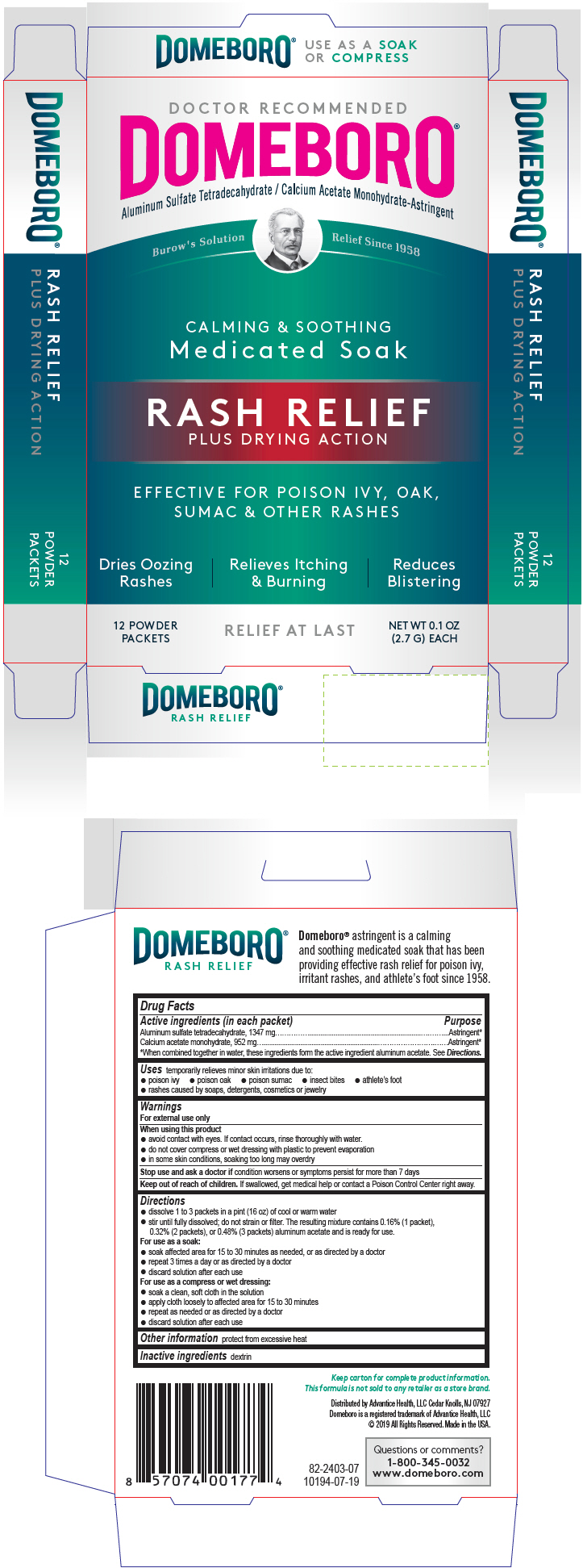 DRUG LABEL: Domeboro
NDC: 16864-240 | Form: POWDER, FOR SOLUTION
Manufacturer: Advantice Health, LLC.
Category: otc | Type: HUMAN OTC DRUG LABEL
Date: 20241212

ACTIVE INGREDIENTS: ALUMINUM SULFATE TETRADECAHYDRATE 1347 mg/1 1; CALCIUM ACETATE MONOHYDRATE 952 mg/1 1
INACTIVE INGREDIENTS: ICODEXTRIN

Domeboro

ACTIVE INGREDIENT

Active Ingredients (in each packet) | Purpose
Aluminum sulfate tetradecahydrate, 1347 mg | Astringent*
Calcium acetate monohydrate, 952 mg | Astringent*
*When combined together in water, these ingredients form the active ingredient aluminum acetate. See Directions.

Uses

temporarily relieves minor skin irritations due to:

- poison ivy
- poison oak
- poison sumac
- insect bites
- athlete's foot
- rashes caused by soaps, detergents, cosmetics, or jewelry

Warnings

For external use only

Whenusing this product

- avoid contact with eyes. If contact occurs, rinse thoroughly with water.
- do not cover compress or wet dressing with plastic to prevent evaporation
- in some skin conditions, soaking too long may overdry

Stop use and ask a doctor ifcondition worsens or symptoms persist for more than 7 days

Keep out of reach of children.If swallowed, get medical help or contact a Poison Control Center right away.

Directions

- dissolve 1 to 3 packets in a pint (16 oz) of cool or warm water
- stir until fully dissolved; do not strain or filter. The resulting mixture contains 0.16% (1 packet), 0.32% (2 packets), or 0.48% (3 packets) aluminum acetate and is ready for use.

For use as a soak:

- soak affected area for 15 to 30 minutes as needed, or as directed by a doctor
- repeat 3 times a day or as directed by a doctor
- discard solution after each use

For use as a compress or wet dressing:

- soak a clean, soft cloth in the solution
- apply cloth loosely to affected area for 15 to 30 minutes
- repeat as needed or as directed by a doctor
- discard solution after each use

STORAGE AND HANDLING

Other informationprotect from excessive heat

Inactive ingredientsdextrin

Questions or comments?

1-800-345-0032
www.domeboro.com

Distributed by Advantice Health, LLC Cedar Knolls, NJ 07927

PRINCIPAL DISPLAY PANEL - 12 Packet Box

DOCTOR RECOMMENDED
DOMEBORO®
Aluminum Sulfate Tetradecahydrate / Calcium Acetate Monohydrate-Astringent

Burow's Solution
Relief Since 1958

CALMING & SOOTHING
Medicated Soak

RASH RELIEF
PLUS DRYING ACTION

EFFECTIVE FOR POISON IVY, OAK,
SUMAC & OTHER RASHES

Dries Oozing
Rashes

Relieves Itching
& Burning

Reduces
Blistering

12 POWDER
PACKETS

RELIEF AT LAST

NET WT 0.1 OZ
(2.7 G) EACH